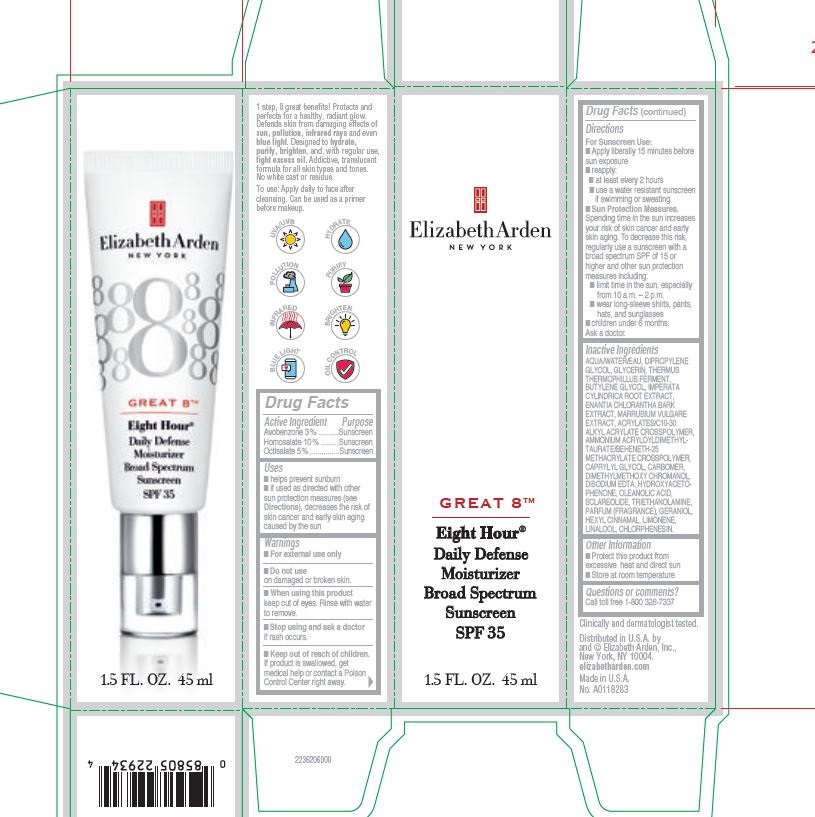 DRUG LABEL: Elizabeth Arden, Great 8, Moisturizer SPF 35
NDC: 10967-665 | Form: EMULSION
Manufacturer: Revlon
Category: otc | Type: HUMAN OTC DRUG LABEL
Date: 20240112

ACTIVE INGREDIENTS: AVOBENZONE 3 mg/1 mL; HOMOSALATE 10 mg/1 mL; OCTISALATE 5 mg/1 mL
INACTIVE INGREDIENTS: TROLAMINE; CHLORPHENESIN; AMMONIUM ACRYLOYLDIMETHYLTAURATE; 2'-HYDROXYACETOPHENONE; DIPROPYLENE GLYCOL; BUTYLENE GLYCOL; IMPERATA CYLINDRICA ROOT; CARBOMER HOMOPOLYMER, UNSPECIFIED TYPE; GLYCERIN; THERMUS THERMOPHILUS LYSATE; CAPRYLYL GLYCOL; OLEANOLIC ACID; CARBOMER INTERPOLYMER TYPE A (55000 CPS); ANNICKIA CHLORANTHA BARK; WATER; EDETATE DISODIUM ANHYDROUS; SCLAREOLIDE

Elizabeth Arden Great 8, Eight Hour Daily Defense Moisturizer Broad Spectrum Sunscreen SPF35

Active Ingredients

Avobenzone 3%

Homosalate 10%

Octisalate 5%

Uses

- helps provent sunburn

- if used as directed with other sun protection measures decreases the risk of cancer and early skin aging caused by the sun

When using this product

keep out of eyes. Rinse with water to remove.

Stop using and ask a doctor

if rash occurs.

Keep out of reach of children.

If product is swalled, get medical help or contact a Poison Control Center right away.

Directions

For Sunscreen Use:

- Apply liberally 15 minutes before sun exposure

- reapply:

at least every 2 hours

use water resistant sunscreen if swimming or sweating

Sun Protection Measures

Spending time in the sun increases your risk of skin cancer and early skin aging. To decrease this risk, regularly use a sunscreen with a broad spectrum SPF of 15 or higher and other sun protection measures including:

limit time in the sun, especially from 10am-2pm

wear long-sleede shirts, pants, hats, and sunglasses

children under 6 months: ask a doctor

Warnings

- For external use only
- Do not Use on damaged or broken skin
- when using this product keep out of eyes. Rinse with water to remove
- stop using and ask a doctor if rash occurs
- keep out of reach of children. If product is swallowed, get medical help or contact a Poison Control Center right away

DOSAGE AND ADMINISTRATION

As needed

INDICATIONS AND USAGE

Sunscreen

INACTIVE INGREDIENT

Aqua/water/eau, dipropylene glycol, glycerin, thermus thermophillus ferment, butylene glycol, imperata cylindrica root extract, enantia chlorantha bark extract, marrubium vulgare extract, acrylates/C10-30 alkyl acrylate crosspolymer, ammonium acryloyldimethyltaurate/beheneth-25 methacrylate crosspolymer, caprylyl glycol, carbomer, dimethylmethoxy chromanol disodium EDTA, hydroxyacetophenone, oleanolic acid, sclareolide, triethanolamine, parfum (fragrance), geraniol, hexyl cinnamal, limonene, linalool, chlorphenesin.